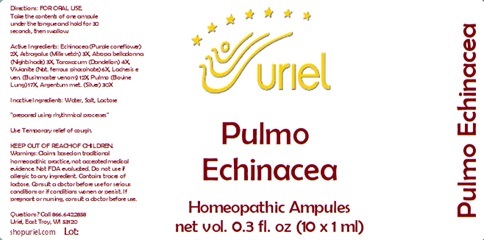 DRUG LABEL: Pulmo Echinacea
NDC: 48951-8085 | Form: LIQUID
Manufacturer: Uriel Pharmacy Inc.
Category: homeopathic | Type: HUMAN OTC DRUG LABEL
Date: 20240126

ACTIVE INGREDIENTS: ECHINACEA ANGUSTIFOLIA 2 [hp_X]/1 mL; ASTRAGALUS PROPINQUUS ROOT 3 [hp_X]/1 mL; ATROPA BELLADONNA 3 [hp_X]/1 mL; TARAXACUM PALUSTRE ROOT 4 [hp_X]/1 mL; FERROSOFERRIC PHOSPHATE 6 [hp_X]/1 mL; LACHESIS MUTA VENOM 12 [hp_X]/1 mL; SUS SCROFA LUNG 17 [hp_X]/1 mL; SILVER 30 [hp_X]/1 mL
INACTIVE INGREDIENTS: WATER; SODIUM CHLORIDE; LACTOSE, UNSPECIFIED FORM

Pulmo Echinacea

INDICATIONS AND USAGE

Directions: FOR ORAL USE.

DOSAGE AND ADMINISTRATION

Take the contents of one ampule under the tongue and hold for 30 seconds, then swallow.

ACTIVE INGREDIENT

Active Ingredients: Echinacea (Purple coneflower) 2X, Astragalus (Milk vetch) 3X, Atropa belladonna (Nightshade) 3X, Taraxacum (Dandelion) 4X, Vivianite (Nat. ferrous phosphate) 6X, Lachesis e ven. (Bushmaster venom) 12X, Pulmo (Bovine Lung) 17X, Argentum met. (Silver) 30X

Inactive Ingredients: Water, Salt, Lactose

"prepared using rhythmical processes"

PURPOSE

Use: Temporary relief of cough.

KEEP OUT OF REACH OF CHILDREN.

WARNINGS

Warnings: Claims based on traditional homeopathic practice, not accepted medical evidence. Not FDA evaluated. Do not use if allergic to any ingredient. Contains traces of lactose. Consult a doctor before use for serious conditions or if conditions worsen or persist. If pregnant or nursing, consult a doctor before use.

QUESTIONS

Questions? Call 866.642.2858 Uriel, East Troy, WI 53120 shopuriel.com Lot: